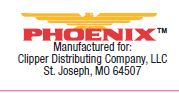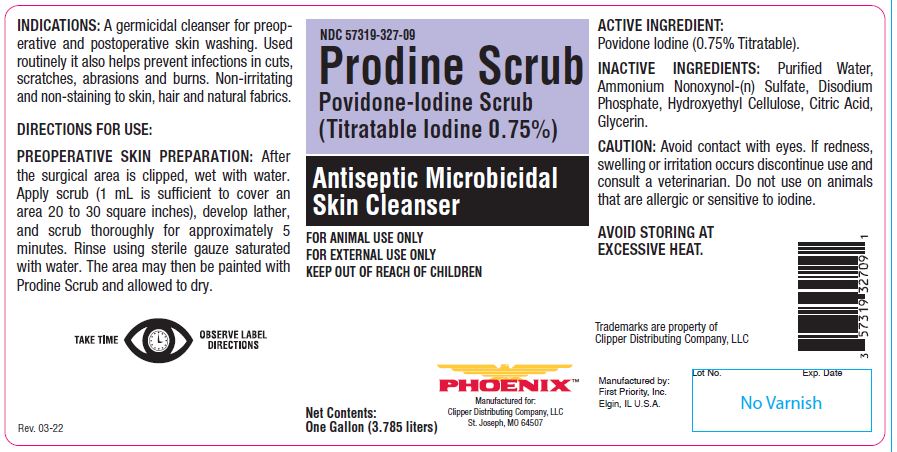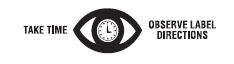 DRUG LABEL: Prodine
NDC: 57319-327 | Form: SOAP
Manufacturer: PHOENIX PHARMACEUTICAL INC./ CLIPPER DISTRIBUTING, INC.
Category: animal | Type: OTC ANIMAL DRUG LABEL
Date: 20250708

ACTIVE INGREDIENTS: POVIDONE-IODINE 46.3 g/1 L

Prodine Scrub
Povidone-Iodine Scrub
(Titratable Iodine 0.75%)

PURPOSE

Antiseptic Microbicidal Skin Cleanser

KEEP OUT OF REACH OF CHILDREN

FOR ANIMAL USE ONLY
FOR EXTERNAL USE ONLY
KEEP OUT OF REACH OF CHILDREN

INDICATIONS:

A germicidal cleanser for preoperative and postoperative skin washing. Used routinely it also helps prevent infections in cuts, scratches, abrasions and burns. Non-irritating and non-staining to skin, hair and natural fabrics.

DIRECTIONS FOR USE:

PREOPERATIVE SKIN PREPARATION: After the surgical area is clipped, wet with water. Apply scrub (1 mL is sufficient to cover an area 20 to 30 square inches), develop lather, and scrub thoroughly for approximately 5 minutes. Rinse using sterile gauze saturated with water. The area may then be painted with Prodine Scrub and allowed to dry.

ACTIVE INGREDIENT:

Povidone Iodine (0.75% Titratable).

INACTIVE INGREDIENTS:

Purified Water, Ammonium Nonoxynol-(n) Sulfate, Disodium Phosphate, Hydroxyethyl Cellulose, Citric Acid, Glycerin.

CAUTION:

Avoid contact with eyes. If redness, swelling or irritation occurs discontinue use and consult a veterinarian. Do not use on animals that are allergic or sensitive to iodine.

STORAGE AND HANDLING

AVOID STORING AT EXCESSIVE HEAT.

Net Contents:

One Gallon (3.785 liters)

INFORMATION FOR OWNERS/CAREGIVERS

Trademarks are property of Clipper Distributing Company, LLC

Manufactured by:
First Priority, Inc.
Elgin, IL U.S.A.